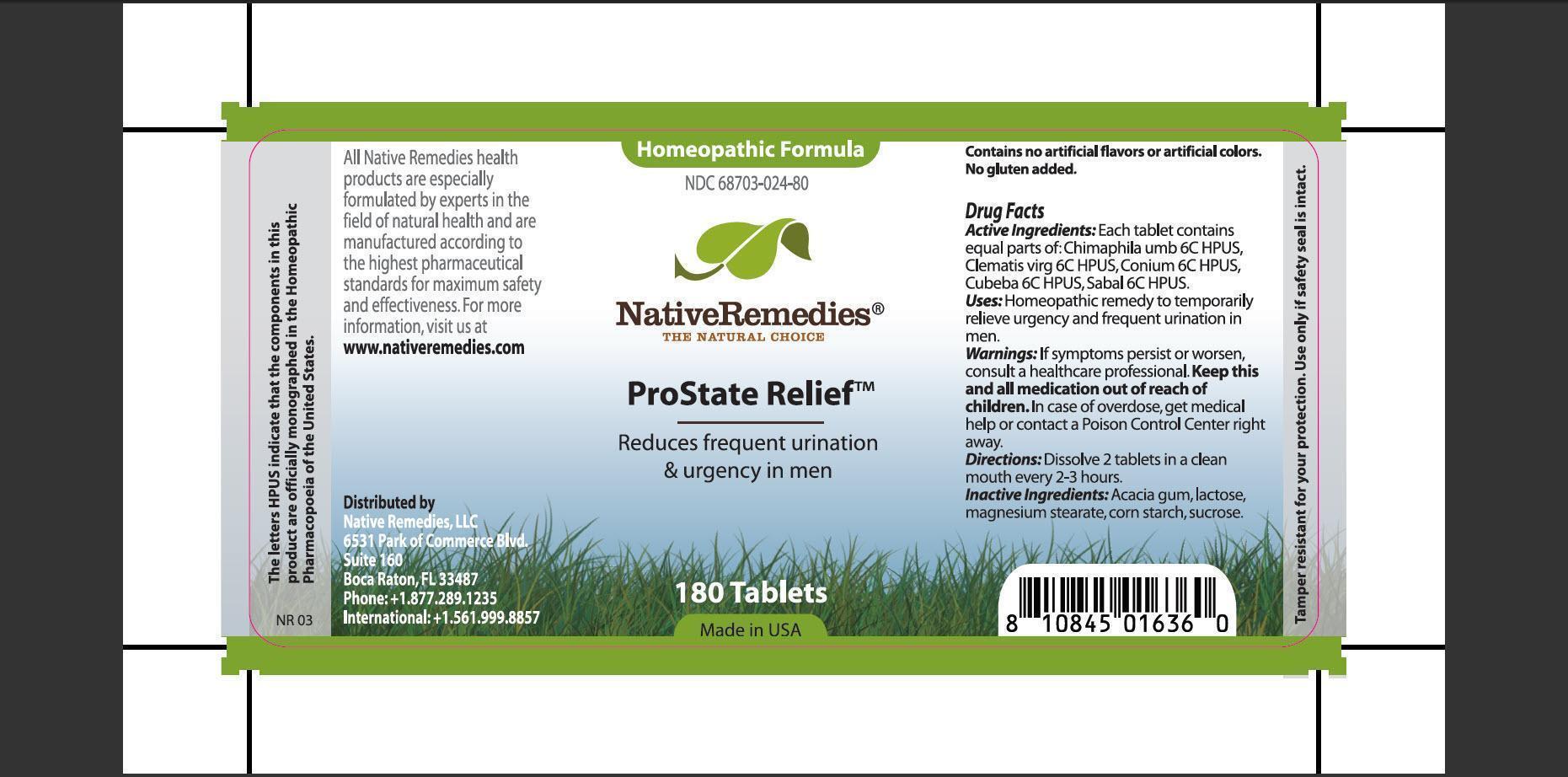 DRUG LABEL: ProState Relief
                
NDC: 68703-024 | Form: TABLET
Manufacturer: Native Remedies, LLC
Category: homeopathic | Type: HUMAN OTC DRUG LABEL
Date: 20130130

ACTIVE INGREDIENTS: CHIMAPHILA UMBELLATA 6 [hp_C]/1 1; CLEMATIS VIRGINIANA TOP 6 [hp_C]/1 1; CONIUM MACULATUM FLOWERING TOP 6 [hp_C]/1 1; PIPER CUBEBA FRUIT 6 [hp_C]/1 1; SAW PALMETTO 6 [hp_C]/1 1
INACTIVE INGREDIENTS: ACACIA; LACTOSE; MAGNESIUM STEARATE; STARCH, CORN; SUCROSE

ProState Relief

PURPOSE

Reduces frequent urination and urgency in men

ACTIVE INGREDIENT

Active Ingredients: Each tablet contains equal parts of: Chimaphila umb 6C HPUS, Clematis virg 6C HPUS, Conium 6C HPUS, Cubeba 6C HPUS, Sabal 6C HPUS.

INDICATIONS AND USAGE

Uses: Homeopathic remedy to temporarily relieve urgency and frequent urination in men.

WARNINGS

Warnings: If symptoms persist or worsen, consult a healthcare professional.

KEEP OUT OF REACH OF CHILDREN

Keep this and all medication out of reach of children.

OVERDOSAGE

In case of overdose, get medical help or contact a Poison Control Center right away.

DOSAGE AND ADMINISTRATION

Directions: Dissolve 2 tablets in a clean mouth every 2-3 hours.

INACTIVE INGREDIENT

Inactive Ingredients: Acacia gum, lactose, magnesium stearate, corn starch, sucrose.

PATIENT COUNSELING INFORMATION

The letters HPUS indicate that the components in this product are officially monographed in the Homeopathic Pharmacopoeia of the United States.

All Native Remedies health products are especially formulated by experts in the fields of natural health and are manufactured according to the highest pharmaceutical standards for maximum safety and effectiveness. For more information, visit us at www.nativeremedies.com

Distributed by
Native Remedies, LLC
6531 Park of Commerce Blvd.
Suite 160
Boca Raton, Fl 33487
Phone:+1.877.289.1235
International:+1.561.999.8857

Contains no artificial flavors or artificial colors. No gluten added.

STORAGE AND HANDLING

Tamper resistant for your protection. Use only if safety seal is intact.